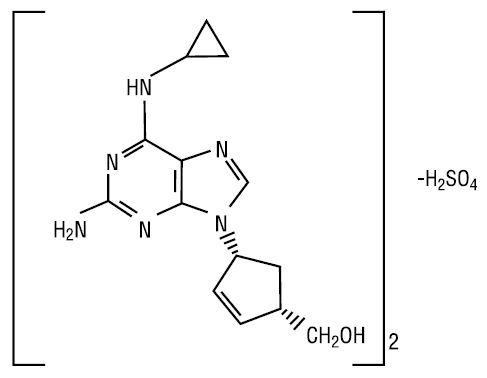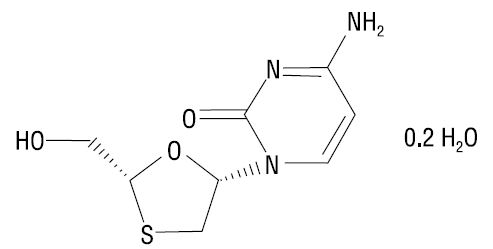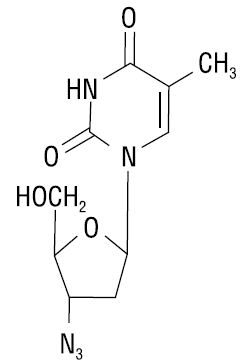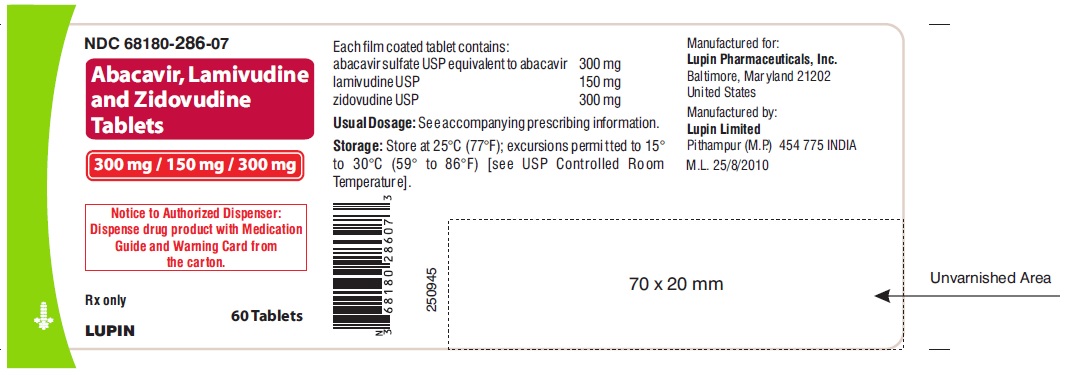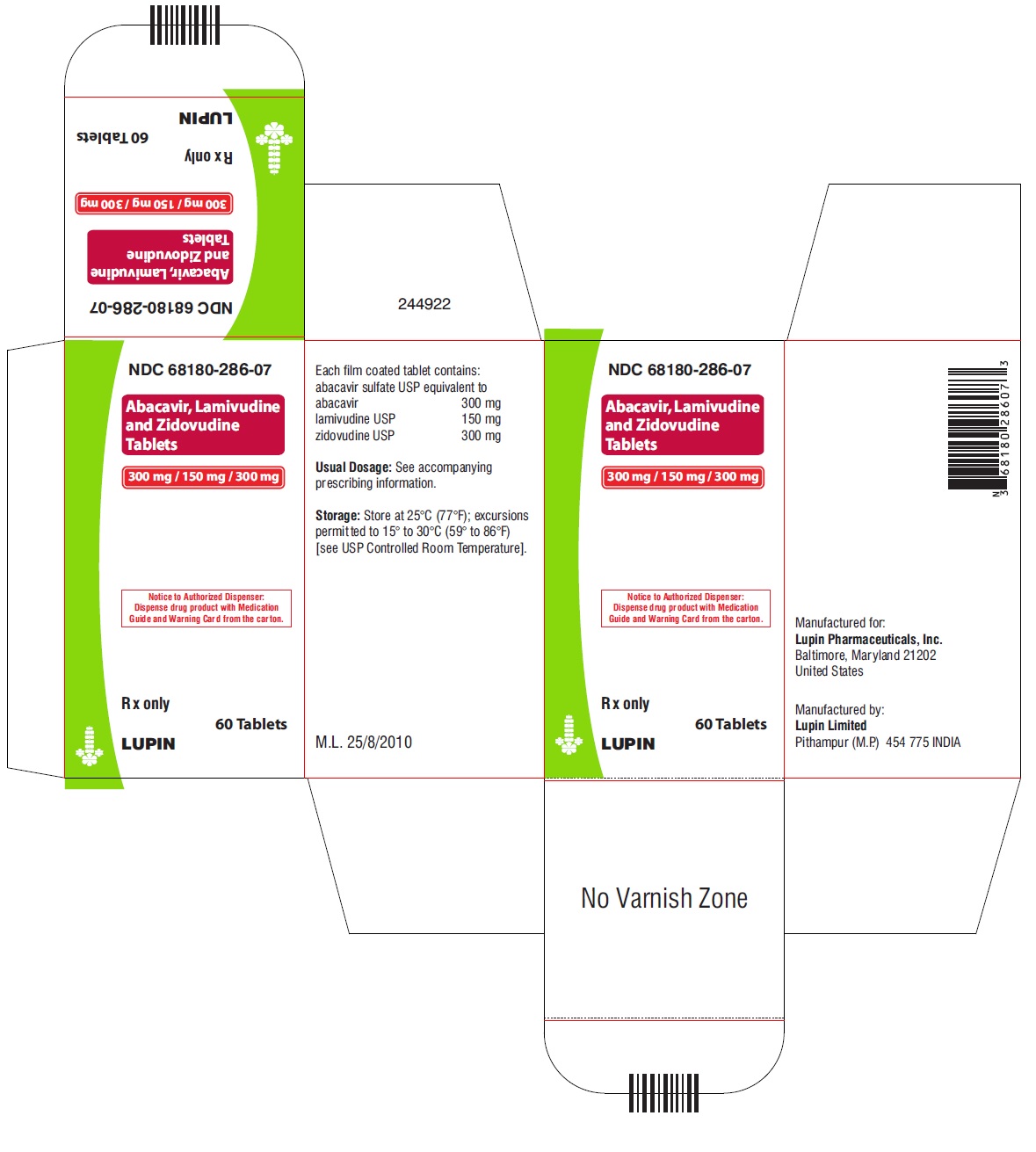 DRUG LABEL: ABACAVIR, LAMIVUDINE AND ZIDOVUDINE
NDC: 68180-286 | Form: TABLET
Manufacturer: Lupin Pharmaceuticals, Inc.
Category: prescription | Type: HUMAN PRESCRIPTION DRUG LABEL
Date: 20231031

ACTIVE INGREDIENTS: LAMIVUDINE 150 mg/1 1; ZIDOVUDINE 300 mg/1 1; ABACAVIR SULFATE 300 mg/1 1
INACTIVE INGREDIENTS: CELLULOSE, MICROCRYSTALLINE; CROSPOVIDONE; FD&C BLUE NO. 2; FERRIC OXIDE YELLOW; MAGNESIUM STEARATE; POLYETHYLENE GLYCOL, UNSPECIFIED; POLYVINYL ALCOHOL, UNSPECIFIED; POVIDONE; TALC; TITANIUM DIOXIDE

HIGHLIGHTS OF PRESCRIBING INFORMATION

These highlights do not include all the information needed to use ABACAVIR, LAMIVUDINE AND ZIDOVUDINE TABLETS safely and effectively. See full prescribing information for ABACAVIR, LAMIVUDINE AND ZIDOVUDINE TABLETS.
ABACAVIR, LAMIVUDINE and ZIDOVUDINE tablets, for oral use
Initial U.S. Approval: 2000

WARNING: HYPERSENSITIVITY REACTIONS, HEMATOLOGIC TOXICITY, MYOPATHY, LACTIC ACIDOSIS AND SEVERE HEPATOMEGALY WITH STEATOSIS, and EXACERBATIONS OF HEPATITIS B

See full prescribing information for complete boxed warning.

Hypersensitivity Reactions

- Serious and sometimes fatal hypersensitivity reactions have occurred with abacavir-containing products. (5.1)
- Hypersensitivity to abacavir is a multi-organ clinical syndrome. (5.1)
- Patients who carry the HLA-B*5701 allele are at a higher risk of experiencing a hypersensitivity reaction to abacavir. (5.1)
- Abacavir, lamivudine and zidovudine tablets are contraindicated in patients with a prior hypersensitivity reaction to abacavir and in HLA-B*5701-positive patients. (4)
- Discontinue abacavir, lamivudine and zidovudine tablets as soon as a hypersensitivity reaction is suspected. Regardless of HLA-B*5701 status, permanently discontinue abacavir, lamivudine and zidovudine tablets if hypersensitivity cannot be ruled out, even when other diagnoses are possible. (5.1)
- Following a hypersensitivity reaction to abacavir, lamivudine and zidovudine tablets NEVER restart abacavir, lamivudine and zidovudine tablets or any other abacavir-containing product. (5.1)

Hematologic Toxicity

- Hematologic toxicity, including neutropenia and anemia, has been associated with the use of zidovudine, a component of abacavir, lamivudine and zidovudine tablets. (5.2)

Myopathy

- Symptomatic myopathy associated with prolonged use of zidovudine. (5.3)

Lactic Acidosis and Severe Hepatomegaly with Steatosis

- Lactic acidosis and severe hepatomegaly with steatosis, including fatal cases, have been reported with the use of nucleoside analogues, including abacavir, lamivudine, and zidovudine (components of abacavir, lamivudine and zidovudine tablets). Suspend treatment if clinical or laboratory findings suggestive of lactic acidosis or pronounced hepatotoxicity occur. (5.4)

Exacerbations of Hepatitis B

- Severe acute exacerbations of hepatitis B have been reported in patients who are co-infected with hepatitis B virus (HBV) and human immunodeficiency virus (HIV-1) and have discontinued lamivudine, a component of abacavir, lamivudine and zidovudine tablets. Monitor hepatic function closely in these patients and, if appropriate, initiate anti-hepatitis B treatment. (5.5)

1 INDICATIONS AND USAGE

Abacavir, lamivudine and zidovudine tablet, a combination of abacavir, lamivudine, and zidovudine, each nucleoside analogue HIV-1 reverse transcriptase inhibitors, is indicated in combination with other antiretroviral agents for the treatment of HIV-1 infection.(1)

2 DOSAGE AND ADMINISTRATION

- Before initiating abacavir, lamivudine and zidovudine tablets, screen for the HLA-B*5701 allele because abacavir, lamivudine and zidovudine tablet contains abacavir. (2.1)
- Adults and pediatric patients weighing at least 40 kg: 1 tablet twice daily. (2.2)
- Because abacavir, lamivudine and zidovudine tablet is a fixed-dose tablet and cannot be dose adjusted, abacavir, lamivudine and zidovudine tablets are not recommended in patients requiring dosage adjustment or patients with hepatic impairment. (2.3, 4)

3 DOSAGE FORMS AND STRENGTHS

- Tablets: 300 mg abacavir, 150 mg lamivudine, and 300 mg zidovudine. (3)

4 CONTRAINDICATIONS

- Presence of HLA-B*5701 allele. (4)
- Prior hypersensitivity reaction to abacavir, lamivudine, or zidovudine (4)
- Moderate or severe hepatic impairment. (4, 8.7)

5 WARNINGS AND PRECAUTIONS

- Hepatic decompensation, some fatal, has occurred in HIV-1/HCV co-infected patients receiving combination antiretroviral therapy and interferon alfa with or without ribavirin. Discontinue abacavir, lamivudine and zidovudine tablets as medically appropriate and consider dose reduction or discontinuation of interferon alfa, ribavirin, or both. (5.6)
- Exacerbation of anemia has been reported in HIV-1/HCV co-infected patients receiving ribavirin and zidovudine. Coadministration of ribavirin and zidovudine is not advised. (5.6)
- Immune reconstitution syndrome and lipoatrophy have been reported in patients treated with combination antiretroviral therapy. (5.7, 5.8)

6 ADVERSE REACTIONS

The most commonly reported adverse reactions (incidence at least 10%) in clinical trials were nausea, headache, malaise and fatigue, and nausea and vomiting. (6.1)

To report SUSPECTED ADVERSE REACTIONS, contact Lupin Pharmaceuticals, Inc. at 1-800-399-2561 or FDA at 1-800-FDA-1088 or www.fda.gov/medwatch.

7 DRUG INTERACTIONS

- Methadone: An increased methadone dose may be required in a small number of patients. (7.1)
- Riociguat: The riociguat dose may need to be reduced. (7.1)
- Sorbitol: Coadministration of lamivudine and sorbitol may decrease lamivudine concentrations; when possible, avoid chronic coadministration. (7.2)
- Agents antagonistic with zidovudine: Concomitant use should be avoided. (7.3)
- Hematologic/bone marrow suppressive/cytotoxic agents: May increase the hematologic toxicity of zidovudine. (7.3)

8 USE IN SPECIFIC POPULATIONS

- Lactation: Women infected with HIV should be instructed not to breastfeed due to potential for HIV transmission. (8.2)

FULL PRESCRIBING INFORMATION

WARNING: HYPERSENSITIVITY REACTIONS, HEMATOLOGIC TOXICITY, MYOPATHY, LACTIC ACIDOSIS AND SEVERE HEPATOMEGALY WITH STEATOSIS, and EXACERBATIONS OF HEPATITIS B

Hypersensitivity Reactions

Serious and sometimes fatal hypersensitivity reactions, with multiple organ involvement, have occurred with abacavir, a component of abacavir, lamivudine and zidovudine tablets. Patients who carry the HLA-B*5701 allele are at a higher risk of a hypersensitivity reaction to abacavir; although, hypersensitivity reactions have occurred in patients who do not carry the HLA-B*5701 allele [see WARNINGS AND PRECAUTIONS (5.1)].

Abacavir, lamivudine and zidovudine tablets are contraindicated in patients with a prior hypersensitivity reaction to abacavir and in HLA-B*5701-positive patients [see CONTRAINDICATIONS (4), WARNINGS AND PRECAUTIONS (5.1)]. All patients should be screened for the HLA-B*5701 allele prior to initiating therapy with abacavir, lamivudine and zidovudine tablets or reinitiation of therapy with abacavir, lamivudine and zidovudine tablets, unless patients have a previously documented HLA-B*5701 allele assessment. Discontinue abacavir, lamivudine and zidovudine tablets immediately if a hypersensitivity reaction is suspected, regardless of HLA-B*5701 status and even when other diagnoses are possible [see CONTRAINDICATIONS (4), WARNINGS AND PRECAUTIONS (5.1)].

Following a hypersensitivity reaction to abacavir, lamivudine and zidovudine tablets, NEVER restart abacavir, lamivudine and zidovudine tablets or any other abacavir-containing product because more severe symptoms, including death, can occur within hours. Similar severe reactions have also occurred rarely following the reintroduction of abacavir-containing products in patients who have no history of abacavir hypersensitivity [see WARNINGS AND PRECAUTIONS (5.1)].

Hematologic Toxicity

Zidovudine, a component of abacavir, lamivudine and zidovudine tablets, has been associated with hematologic toxicity, including neutropenia and severe anemia, particularly in patients with advanced Human Immunodeficiency Virus (HIV-1) disease [see WARNINGS AND PRECAUTIONS (5.2)].

Myopathy

Prolonged use of zidovudine has been associated with symptomatic myopathy [see WARNINGS AND PRECAUTIONS (5.3)].

Lactic Acidosis and Severe Hepatomegaly with Steatosis

Lactic acidosis and severe hepatomegaly with steatosis, including fatal cases, have been reported with the use of nucleoside analogues, including abacavir, lamivudine, and zidovudine (components of abacavir, lamivudine and zidovudine tablets). Discontinue abacavir, lamivudine and zidovudine tablets if clinical or laboratory findings suggestive of lactic acidosis or pronounced hepatotoxicity occur [see WARNINGS AND PRECAUTIONS (5.4)].

Exacerbations of Hepatitis B

Severe acute exacerbations of hepatitis B have been reported in patients who are co-infected with hepatitis B virus (HBV) and HIV-1 and have discontinued lamivudine, a component of abacavir, lamivudine and zidovudine tablets. Hepatic function should be monitored closely with both clinical and laboratory follow-up for at least several months in patients who discontinue abacavir, lamivudine and zidovudine tablets and are co-infected with HIV-1 and HBV. If appropriate, initiation of anti-hepatitis B therapy may be warranted [see WARNINGS AND PRECAUTIONS (5.5)].

1 INDICATIONS AND USAGE

Abacavir, lamivudine and zidovudine tablet is indicated in combination with other antiretrovirals or alone for the treatment of human immunodeficiency virus type 1 (HIV-1) infection.

Limitations of Use:

- Limited data exist on the use of abacavir, lamivudine and zidovudine tablets alone in patients with higher baseline viral load levels (greater than 100,000 copies per mL) [see CLINICAL STUDIES (14)] .

2 DOSAGE AND ADMINISTRATION

2.1 Screening for HLA-B*5701 Allele prior to Starting Abacavir, Lamivudine and Zidovudine Tablets

Screen for the HLA-B*5701 allele prior to initiating therapy with abacavir, lamivudine and zidovudine tablets [see BOXED WARNING, WARNINGS AND PRECAUTIONS (5.1)].

2.2 Recommended Dosage for Adults and Pediatric Patients Weighing at Least 40 kg

The recommended dosage of abacavir, lamivudine and zidovudine tablet is one tablet taken orally twice daily with or without food.

2.3 Not Recommended Due to Lack of Dosage Adjustment

Because abacavir, lamivudine and zidovudine tablet is a fixed-dose tablet and cannot be dose adjusted, abacavir, lamivudine and zidovudine tablet is not recommended for:

- pediatric patients who weigh less than 40 kg [see USE IN SPECIFIC POPULATIONS (8.4)].
- patients with creatinine clearance less than 50 mL per minute [see USE IN SPECIFIC POPULATIONS (8.6)].
- patients with mild hepatic impairment. Abacavir, lamivudine and zidovudine tablet is contraindicated in patients with moderate or severe hepatic impairment [see CONTRAINDICATIONS (4), USE IN SPECIFIC POPULATIONS (8.7)] .

3 DOSAGE FORMS AND STRENGTHS

Abacavir, lamivudine and zidovudine tablets contain 300 mg of abacavir as abacavir sulfate, 150 mg of lamivudine, and 300 mg of zidovudine. The tablets are blue-green colored, oval shaped, biconvex, film-coated, debossed with "LU" on one side and "N51" on the other side.

4 CONTRAINDICATIONS

Abacavir, lamivudine and zidovudine tablets are contraindicated in patients:

- who have the HLA-B*5701 allele [see WARNINGS AND PRECAUTIONS (5.1)].
- with prior hypersensitivity reaction to abacavir [see WARNINGS AND PRECAUTIONS (5.1)], lamivudine, or zidovudine.
- with moderate or severe hepatic impairment [see USE IN SPECIFIC POPULATIONS (8.7)] .

5 WARNINGS AND PRECAUTIONS

5.1 Hypersensitivity Reactions

Serious and sometimes fatal hypersensitivity reactions have occurred with abacavir, a component of abacavir, lamivudine and zidovudine tablets. These hypersensitivity reactions have included multi-organ failure and anaphylaxis and typically occurred within the first 6 weeks of treatment with abacavir (median time to onset was 9 days); although abacavir hypersensitivity reactions have occurred any time during treatment [see ADVERSE REACTIONS (6.1)]. Patients who carry the HLA-B*5701 allele are at a higher risk of abacavir hypersensitivity reactions; although, patients who do not carry the HLA-B*5701 allele have developed hypersensitivity reactions. Hypersensitivity to abacavir was reported in approximately 206 (8%) of 2,670 patients in 9 clinical trials with abacavir-containing products where HLA-B*5701 screening was not performed. The incidence of suspected abacavir hypersensitivity reactions in clinical trials was 1% when subjects carrying the HLA-B*5701 allele were excluded. In any patient treated with abacavir, the clinical diagnosis of hypersensitivity reaction must remain the basis of clinical decision making.

Due to the potential for severe, serious, and possibly fatal hypersensitivity reactions with abacavir:

- All patients should be screened for the HLA-B*5701 allele prior to initiating therapy with abacavir, lamivudine and zidovudine tablets or reinitiation of therapy with abacavir, lamivudine and zidovudine tablets, unless patients have a previously documented HLA-B*5701 allele assessment.
- Abacavir, lamivudine, and zidovudine tablets are contraindicated in patients with a prior hypersensitivity reaction to abacavir and in HLA-B*5701-positive patients.
- Before starting abacavir, lamivudine and zidovudine tablets, review medical history for prior exposure to any abacavir-containing product. NEVER restart abacavir, lamivudine and zidovudine tablets or any other abacavir-containing product following a hypersensitivity reaction to abacavir, regardless of HLA-B*5701 status.
- To reduce the risk of a life-threatening hypersensitivity reaction, regardless of HLA-B*5701 status, discontinue abacavir, lamivudine and zidovudine tablets immediately if a hypersensitivity reaction is suspected, even when other diagnoses are possible (e.g., acute onset respiratory diseases such as pneumonia, bronchitis, pharyngitis, or influenza; gastroenteritis; or reactions to other medications).
- If a hypersensitivity reaction cannot be ruled out, do not restart abacavir, lamivudine and zidovudine tablets or any other abacavir-containing products because more severe symptoms, which may include life-threatening hypotension and death, can occur within hours.
- If a hypersensitivity reaction is ruled out, patients may restart abacavir, lamivudine and zidovudine tablets. Rarely, patients who have stopped abacavir for reasons other than symptoms of hypersensitivity have also experienced life-threatening reactions within hours of reinitiating abacavir therapy. Therefore, reintroduction of abacavir, lamivudine and zidovudine tablets or any other abacavir-containing product is recommended only if medical care can be readily accessed.
- A Medication Guide and Warning Card that provide information about recognition of abacavir hypersensitivity reactions should be dispensed with each new prescription and refill.

5.2 Hematologic Toxicity/Bone Marrow Suppression

Zidovudine, a component of abacavir, lamivudine and zidovudine tablet, has been associated with hematologic toxicity including neutropenia and anemia, particularly in patients with advanced HIV-1 disease. Abacavir, lamivudine and zidovudine tablets should be used with caution in patients who have bone marrow compromise evidenced by granulocyte count less than 1,000 cells per mm^3 or hemoglobin less than 9.5 grams per dL [see ADVERSE REACTIONS (6.1)].

Frequent blood counts are strongly recommended in patients with advanced HIV-1 disease who are treated with abacavir, lamivudine and zidovudine tablets. Periodic blood counts are recommended for other HIV-1-infected patients. If anemia or neutropenia develops, dosage interruption may be needed.

5.3 Myopathy

Myopathy and myositis, with pathological changes similar to that produced by HIV-1 disease, have been associated with prolonged use of zidovudine, and therefore may occur with therapy with abacavir, lamivudine and zidovudine tablets.

5.4 Lactic Acidosis and Severe Hepatomegaly with Steatosis

Lactic acidosis and severe hepatomegaly with steatosis, including fatal cases, have been reported with the use of nucleoside analogues, including abacavir, lamivudine and zidovudine (components of abacavir, lamivudine and zidovudine tablets). A majority of these cases have been in women. Female sex and obesity may be risk factors for the development of lactic acidosis and severe hepatomegaly with steatosis in patients treated with antiretroviral nucleoside analogues. See full prescribing information for ZIAGEN® (abacavir), EPIVIR® (lamivudine), and RETROVIR® (zidovudine). Treatment with abacavir, lamivudine and zidovudine tablets should be suspended in any patient who develops clinical or laboratory findings suggestive of lactic acidosis or pronounced hepatotoxicity (which may include hepatomegaly and steatosis even in the absence of marked transaminase elevations).

5.5 Patients with Hepatitis B Virus Co-infection

Posttreatment Exacerbations of Hepatitis

Clinical and laboratory evidence of exacerbations of hepatitis have occurred after discontinuation of lamivudine. See full prescribing information for EPIVIR® (lamivudine). Patients should be closely monitored with both clinical and laboratory follow-up for at least several months after stopping treatment.

Emergence of Lamivudine-Resistant HBV

Safety and efficacy of lamivudine have not been established for treatment of chronic hepatitis B in subjects dually infected with HIV-1 and HBV. Emergence of hepatitis B virus variants associated with resistance to lamivudine has been reported in HIV–1-infected subjects who have received lamivudine-containing antiretroviral regimens in the presence of concurrent infection with hepatitis B virus. See full prescribing information for EPIVIR® (lamivudine).

5.6 Use with Interferon- and Ribavirin-Based Regimens

Patients receiving interferon alfa with or without ribavirin and abacavir, lamivudine and zidovudine tablets should be closely monitored for treatment-associated toxicities, especially hepatic decompensation, neutropenia, and anemia. See full prescribing information for RETROVIR® (zidovudine). Discontinuation of abacavir, lamivudine and zidovudine tablets should be considered as medically appropriate. Dose reduction or discontinuation of interferon alfa, ribavirin, or both should also be considered if worsening clinical toxicities are observed, including hepatic decompensation (e.g., Child-Pugh greater than 6) (see full prescribing information for interferon and ribavirin).

Exacerbation of anemia has been reported in HIV-1/HCV co-infected patients receiving ribavirin and zidovudine. Coadministration of ribavirin and abacavir, lamivudine and zidovudine tablet is not advised.

5.7 Immune Reconstitution Syndrome

Immune reconstitution syndrome has been reported in patients treated with combination antiretroviral therapy, including abacavir, lamivudine and zidovudine tablets. During the initial phase of combination antiretroviral treatment, patients whose immune systems respond may develop an inflammatory response to indolent or residual opportunistic infections (such as Mycobacterium avium infection, cytomegalovirus, Pneumocystis jirovecii pneumonia [PCP], or tuberculosis), which may necessitate further evaluation and treatment.

Autoimmune disorders (such as Graves' disease, polymyositis, and Guillain-BarrÉ syndrome) have also been reported to occur in the setting of immune reconstitution; however, the time to onset is more variable, and can occur many months after initiation of treatment.

5.8 Lipoatrophy

Treatment with zidovudine, a component of abacavir, lamivudine and zidovudine tablets, has been associated with loss of subcutaneous fat. The incidence and severity of lipoatrophy are related to cumulative exposure. This fat loss, which is most evident in the face, limbs, and buttocks, may be only partially reversible and improvement may take months to years after switching to a non-zidovudine-containing regimen. Patients should be regularly assessed for signs of lipoatrophy during therapy with zidovudine-containing products, and if feasible, therapy should be switched to an alternative regimen if there is suspicion of lipoatrophy.

5.9 Myocardial Infarction

Several prospective, observational, epidemiological studies have reported an association with the use of abacavir and the risk of myocardial infarction (MI). Meta-analyses of randomized, controlled clinical trials have observed no excess risk of MI in abacavir-treated subjects as compared with control subjects. To date, there is no established biological mechanism to explain a potential increase in risk. In totality, the available data from the observational studies and from controlled clinical trials show inconsistency; therefore, evidence for a causal relationship between abacavir treatment and the risk of MI is inconclusive.

As a precaution, the underlying risk of coronary heart disease should be considered when prescribing antiretroviral therapies, including abacavir, and action taken to minimize all modifiable risk factors (e.g., hypertension, hyperlipidemia, diabetes mellitus, smoking).

5.10 Therapy-Experienced Patients

In clinical trials, subjects with prolonged prior nucleoside reverse transcriptase inhibitor (NRTI) exposure or who had HIV-1 isolates that contained multiple mutations conferring resistance to NRTIs had limited response to abacavir. The potential for cross-resistance between abacavir and other NRTIs should be considered when choosing new therapeutic regimens in therapy- experienced patients [see Microbiology (12.4)].

6 ADVERSE REACTIONS

The following adverse reactions are discussed in other sections of the labeling:

- Serious and sometimes fatal hypersensitivity reactions [see BOXED WARNING, WARNINGS AND PRECAUTIONS (5.1)] .
- Hematologic toxicity, including neutropenia and anemia [see BOXED WARNING, WARNINGS AND PRECAUTIONS (5.2)] .
- Symptomatic myopathy [see BOXED WARNING, WARNINGS AND PRECAUTIONS (5.3)] .
- Lactic acidosis and severe hepatomegaly with steatosis [see BOXED WARNING, WARNINGS AND PRECAUTIONS (5.4)] .
- Exacerbations of hepatitis B [seeBOXED WARNING, WARNINGS AND PRECAUTIONS (5.5)] .
- Hepatic decompensation in patients co-infected with HIV-1 and hepatitis C [see WARNINGS AND PRECAUTIONS (5.6)] .
- Exacerbation of anemia in HIV-1/HCV co-infected patients receiving ribavirin and zidovudine [see WARNINGS AND PRECAUTIONS (5.6)] .
- Immune reconstitution syndrome [see WARNINGS AND PRECAUTIONS (5.7)] .
- Lipoatrophy [see WARNINGS AND PRECAUTIONS (5.8)] .
- Myocardial infarction [see WARNINGS AND PRECAUTIONS (5.9)] .

6.1 Clinical Trials Experience

Because clinical trials are conducted under widely varying conditions, adverse reaction rates observed in the clinical trials of a drug cannot be directly compared with rates in the clinical trials of another drug and may not reflect the rates observed in clinical practice.

Serious and Fatal Abacavir-Associated Hypersensitivity Reactions

In clinical trials, serious and sometimes fatal hypersensitivity reactions have occurred with abacavir, a component of abacavir, lamivudine and zidovudine tablets [see BOXED WARNING, WARNINGS AND PRECAUTIONS (5.1)]. These reactions have been characterized by 2 or more of the following signs or symptoms: (1) fever; (2) rash; (3) gastrointestinal symptoms (including nausea, vomiting, diarrhea, or abdominal pain); (4) constitutional symptoms (including generalized malaise, fatigue, or achiness); (5) respiratory symptoms (including dyspnea, cough, or pharyngitis). Almost all abacavir hypersensitivity reactions include fever and/or rash as part of the syndrome.

Other signs and symptoms have included lethargy, headache, myalgia, edema, arthralgia, and paresthesia. Anaphylaxis, liver failure, renal failure, hypotension, adult respiratory distress syndrome, respiratory failure, myolysis, and death have occurred in association with these hypersensitivity reactions. Physical findings have included lymphadenopathy, mucous membrane lesions (conjunctivitis and mouth ulcerations), and maculopapular or urticarial rash (although some patients had other types of rashes and others did not have a rash). There were reports of erythema multiforme. Laboratory abnormalities included elevated liver chemistries, elevated creatine phosphokinase, elevated creatinine, and lymphopenia, and abnormal chest x-ray findings (predominantly infiltrates, which were localized).

Additional Adverse Reactions with Use of Abacavir, Lamivudine and Zidovudine Tablets

Treatment-emergent clinical adverse reactions (rated by the investigator as moderate or severe) with a frequency greater than or equal to 5% during therapy with abacavir 300 mg twice daily, lamivudine 150 mg twice daily, and zidovudine 300 mg twice daily compared with indinavir 800 mg 3 times daily, lamivudine 150 mg twice daily, and zidovudine 300 mg twice daily from CNA3005 are listed in Table 1.

Table 1. Treatment-Emergent (All Causality) Adverse Reactions of at Least Moderate Intensity (Grades 2 to 4, Greater than or Equal to 5% Frequency) in Therapy-Naive Adults (CNA3005) through 48 Weeks of Treatment
Adverse Reaction | ZIAGEN® plus Lamivudine/Zidovudine (n=262) | Indinavir plus Lamivudine/Zidovudine (n=264)
Nausea | 19% | 17%
Headache | 13% | 9%
Malaise and fatigue | 12% | 12%
Nausea and vomiting | 10% | 10%
Hypersensitivity reaction | 8% | 2%
Diarrhea | 7% | 5%
Fever and/or chills | 6% | 3%
Depressive disorders | 6% | 4%
Musculoskeletal pain | 5% | 7%
Skin rashes | 5% | 4%
Ear/nose/throat infections | 5% | 4%
Viral respiratory infections | 5% | 5%
Anxiety | 5% | 3%
Renal signs/symptoms | <1% | 5%
Pain (non-site-specific) | <1% | 5%

Five subjects receiving abacavir in CNA3005 experienced worsening of pre-existing depression compared to none in the indinavir arm. The background rates of pre-existing depression were similar in the 2 treatment arms.

Laboratory Abnormalities

Laboratory abnormalities in CNA3005 are listed in Table 2.

Table 2. Treatment-Emergent Laboratory Abnormalities (Grades 3/4) in CNA3005
Laboratory Parameter | ZIAGEN® plus Lamivudine/Zidovudine (n = 262) | Indinavir plus Lamivudine/Zidovudine (n = 264)
Elevated CPK (>4 x ULN) | 18 (7%) | 18 (7%)
ALT (>5.0 x ULN) | 16 (6%) | 16 (6%)
Neutropenia (<750/mm^3) | 13 (5%) | 13 (5%)
Hypertriglyceridemia (>750 mg/dL) | 5 (2%) | 3 (1%)
Hyperamylasemia (>2.0 x ULN) | 5 (2%) | 1 (<1%)
Hyperglycemia (>13.9 mmol/L) | 2 (<1%) | 2 (<1%)
Anemia (Hgb ≤6.9 g/dL) | 0 (0%) | 3 (1%)
ULN = Upper limit of normal.
n = Number of subjects assessed.

Other Adverse Events

In addition to adverse reactions in Tables 1 and 2, other adverse events observed in the expanded access program for abacavir were pancreatitis and increased GGT.

6.2 Postmarketing Experience

The following adverse reactions have been identified during postmarketing use. Because these reactions are reported voluntarily from a population of unknown size, it is not always possible to reliably estimate their frequency or establish a causal relationship to drug exposure.

Abacavir

Cardiovascular:

Myocardial infarction.

Skin:

Suspected Stevens-Johnson syndrome (SJS) and toxic epidermal necrolysis (TEN) have been reported in patients receiving abacavir primarily in combination with medications known to be associated with SJS and TEN, respectively. Because of the overlap of clinical signs and symptoms between hypersensitivity to abacavir and SJS and TEN, and the possibility of multiple drug sensitivities in some patients, abacavir should be discontinued and not restarted in such cases. There have also been reports of erythema multiforme with abacavir use [see ADVERSE REACTIONS (6.1)].

Abacavir, Lamivudine, and/or Zidovudine

Body as a Whole:

Redistribution/accumulation of body fat.

Cardiovascular:

Cardiomyopathy.

Digestive:

Stomatitis.

Endocrine and Metabolic:

Gynecomastia.

Gastrointestinal:

Anorexia and/or decreased appetite, abdominal pain, dyspepsia, oral mucosal pigmentation.

General:

Vasculitis, weakness.

Hemic and Lymphatic:

Aplastic anemia, anemia (including pure red cell aplasia and severe anemias progressing on therapy), lymphadenopathy, splenomegaly, thrombocytopenia.

Hepatic:

Lactic acidosis and hepatic steatosis [see WARNINGS AND PRECAUTIONS (5.4)], elevated bilirubin, elevated transaminases, posttreatment exacerbations of hepatitis B [see WARNINGS AND PRECAUTIONS (5.5)].

Hypersensitivity:

Sensitization reactions (including anaphylaxis), urticaria.

Musculoskeletal:

Arthralgia, myalgia, muscle weakness, rhabdomyolysis.

Nervous:

Dizziness, paresthesia, peripheral neuropathy, seizures.

Psychiatric:

Insomnia and other sleep disorders.

Respiratory:

Abnormal breath sounds/wheezing.

Skin:

Alopecia, erythema multiforme, Stevens-Johnson syndrome.

7 DRUG INTERACTIONS

7.1 Abacavir

Methadone

In a trial of 11 HIV-1-infected subjects receiving methadone-maintenance therapy with 600 mg of ZIAGEN® twice daily (twice the currently recommended dose), oral methadone clearance increased [see CLINICAL PHARMACOLOGY (12.3)]. This alteration will not result in a methadone dose modification in the majority of patients; however, an increased methadone dose may be required in a small number of patients.

Riociguat

Coadministration with fixed-dose abacavir/dolutegravir/lamivudine resulted in increased riociguat exposure, which may increase the risk of riociguat adverse reactions [see Clinical Pharmacology (12.3)]. The riociguat dose may need to be reduced. See full prescribing information for ADEMPAS (riociguat).

7.2 Lamivudine

Sorbitol

Coadministration of single doses of lamivudine and sorbitol resulted in a sorbitol dose-dependent reduction in lamivudine exposures. When possible, avoid use of sorbitol-containing medicines with lamivudine-containing medicines [see CLINICAL PHARMACOLOGY (12.3)].

7.3 Zidovudine

Agents Antagonistic with Zidovudine

Concomitant use of zidovudine with the following drugs should be avoided since an antagonistic relationship has been demonstrated in vitro:

- Stavudine
- Doxorubicin
- Nucleoside analogues, e.g., ribavirin

Hematologic/Bone Marrow Suppressive/Cytotoxic Agents

Coadministration with the following drugs may increase the hematologic toxicity of zidovudine:

- Ganciclovir
- Interferon alfa
- Ribavirin
- Other bone marrow suppressive or cytotoxic agents

8 USE IN SPECIFIC POPULATIONS

8.1 Pregnancy

Pregnancy Exposure Registry

There is a pregnancy exposure registry that monitors pregnancy outcomes in women exposed to abacavir, lamivudine and zidovudine tablets during pregnancy. Healthcare providers are encouraged to register patients by calling the Antiretroviral Pregnancy Registry (APR) at 1-800-258-4263.

Risk Summary

Available data from the APR show no difference in the overall risk of birth defects for abacavir, lamivudine, or zidovudine compared with the background rate for birth defects of 2.7% in the Metropolitan Atlanta Congenital Defects Program (MACDP) reference population [see Data]. The APR uses the MACDP as the U.S. reference population for birth defects in the general population. The MACDP evaluates women and infants from a limited geographic area and does not include outcomes for births that occurred at less than 20 weeks' gestation. The rate of miscarriage is not reported in the APR. The estimated background rate of miscarriage in clinically recognized pregnancies in the U.S. general population is 15% to 20%. The background risk for major birth defects and miscarriage for the indicated population is unknown.

Hyperlactatemia, which may be due to mitochondrial dysfunction, has been reported in infants with in utero exposure to zidovudine-containing products. These events were transient and asymptomatic in most cases. There have been few reports of developmental delay, seizures, and other neurological disease. However, a causal relationship between these events and exposure to zidovudine-containing products in utero or peri-partum has not been established (see Data).

In animal reproduction studies, oral administration of abacavir to pregnant rats during organogenesis resulted in fetal malformations and other embryonic and fetal toxicities at exposures 35 times the human exposure (AUC) at the recommended clinical daily dose. However, no adverse developmental effects were observed following oral administration of abacavir to pregnant rabbits during organogenesis, at exposures approximately 9 times the human exposure (AUC) at the recommended clinical dose. Oral administration of lamivudine to pregnant rabbits during organogenesis resulted in embryolethality at systemic exposure (AUC) similar to the recommended clinical dose; however, no adverse development effects were observed with oral administration of lamivudine to pregnant rats during organogenesis at plasma concentrations (Cmax) 35 times the recommended clinical dose. Administration of oral zidovudine to female rats prior to mating and throughout gestation resulted in embryotoxicity at doses that produced systemic exposure (AUC) approximately 33 times higher than exposure at the recommended clinical dose. However, no embryotoxicity was observed after oral administration of zidovudine to pregnant rats during organogenesis at doses that produced systemic exposure (AUC) approximately 117 times higher than exposures at the recommended clinical dose. Administration of oral zidovudine to pregnant rabbits during organogenesis resulted in embryotoxicity at doses that produced systemic exposure (AUC) approximately 108 times higher than exposure at the recommended clinical dose. However, no embryotoxicity was observed at doses that produced systemic exposure (AUC) approximately 23 times higher than exposures at the recommended clinical dose (see Data).

Data

Human Data:

Abacavir

Based on prospective reports to the APR of exposures to abacavir during pregnancy resulting in live births (including over 1,300 exposed in the first trimester and over 1,300 exposed in the second/third trimester), there was no difference between the overall risk of birth defects for abacavir compared with the background birth defect rate of 2.7% in a U.S. reference population of the MACDP. The prevalence of defects in live births was 3.2% (95% CI: 2.3% to 4.3%) following first trimester exposure to abacavir-containing regimens and 2.9% (95% CI: 2.1% to 4%) following second/third trimester exposure to abacavir-containing regimens.

Abacavir has been shown to cross the placenta and concentrations in neonatal plasma at birth were essentially equal to those in maternal plasma at delivery [see CLINICAL PHARMACOLOGY (12.3)].

Lamivudine

Based on prospective reports to the APR of of exposures to lamivudine during pregnancy resulting in live births (including over 5300 exposed in the first trimester and over 7,400 exposed in the second/third trimester), there was no difference between the overall risk of birth defects for lamivudine compared with the background birth defect rate of 2.7% in a U.S. reference population of the MACDP. The prevalence of birth defects in live births was 3.1% (95% CI: 2.7% to 3.6%) following first trimester exposure to lamivudine-containing regimens and 2.9% (95% CI: 2.5% to 3.3%) following second/third trimester exposure to lamivudine-containing regimens..

Lamivudine pharmacokinetics were studied in pregnant women during 2 clinical trials conducted in South Africa. The trials assessed pharmacokinetics in 16 women at 36 weeks' gestation using 150 mg lamivudine twice daily with zidovudine, 10 women at 38 weeks' gestation using 150 mg lamivudine twice daily with zidovudine, and 10 women at 38 weeks' gestation using lamivudine 300 mg twice daily without other antiretrovirals. These trials were not designed or powered to provide efficacy information. Lamivudine concentrations were generally similar in maternal, neonatal, and umbilical cord serum samples. In a subset of subjects, amniotic fluid specimens were collected following natural rupture of membranes and confirmed that lamivudine crosses the placenta in humans. Based on limited data at delivery, median (range) amniotic fluid concentrations of lamivudine were 3.9 (1.2 to 12.8)–fold greater compared with paired maternal serum concentration (n = 8).

Zidovudine

Based on prospective reports to the APR of exposures to zidovudine during pregnancy resulting in live births (including over 4,200 exposed in the first trimester and over 9,700 exposed in the second/third trimester), there was no difference between the overall risk of birth defects for zidovudine compared with the background birth defect rate of 2.7% in a U.S. reference population of the MACDP. The prevalence of birth defects in live births was 3.2% (95% CI: 2.7% to 3.8%) following first trimester exposure to zidovudine-containing regimens and 2.8% (95% CI: 2.5% to 3.1%) following second/third trimester exposure to zidovudine-containing regimens.

A randomized, double-blind, placebo-controlled trial was conducted in HIV-1-infected pregnant women to determine the utility of zidovudine for the prevention of maternal-fetal HIV-1 transmission. Zidovudine treatment during pregnancy reduced the rate of maternal-fetal HIV-1 transmission from 24.9% for infants born to placebo-treated mothers to 7.8% for infants born to mothers treated with zidovudine. There were no differences in pregnancy-related adverse events between the treatment groups. Of the 363 neonates that were evaluated, congenital abnormalities occurred with similar frequency between neonates born to mothers who received zidovudine and neonates born to mothers who received placebo. The observed abnormalities included problems in embryogenesis (prior to 14 weeks) or were recognized on ultrasound before or immediately after initiation of trial drug. See full prescribing information for RETROVIR® (zidovudine) and COMBIVIR® (lamivudine and zidovudine).

Zidovudine has been shown to cross the placenta and concentrations in neonatal plasma at birth were essentially equal to those in maternal plasma at delivery [see CLINICAL PHARMACOLOGY (12.3)].

There have been reports of mild, transient elevations in serum lactate levels, which may be due to mitochondrial dysfunction, in neonates and infants exposed in utero or peri-partum to zidovudine-containing products. There have been few reports of developmental delay, seizures, and other neurological disease. However, a causal relationship between these events and exposure to zidovudine-containing products in utero or peri-partum has not been established. The clinical relevance of transient elevations in serum lactate is unknown.

Animal Data:

Abacavir

Abacavir was administered orally to pregnant rats (at 100, 300, and 1,000 mg per kg per day) and rabbits (at 125, 350, or 700 mg per kg per day) during organogenesis (on Gestation Days 6 through 17 and 6 through 20, respectively). Fetal malformations (increased incidences of fetal anasarca and skeletal malformations) or developmental toxicity (decreased fetal body weight and crown-rump length) were observed in rats at doses up to 1,000 mg per kg per day, resulting in exposures approximately 35 times the human exposure (AUC) at the recommended daily dose. No developmental effects were observed in rats at 100 mg per kg per day, resulting in exposures (AUC) 3.5 times the human exposure at the recommended daily dose. In a fertility and early embryo-fetal development study conducted in rats (at 60, 160, or 500 mg per kg per day), embryonic and fetal toxicities (increased resorptions, decreased fetal body weights) or toxicities to the offspring (increased incidence of stillbirth and lower body weights) occurred at doses up to 500 mg per kg per day. No developmental effects were observed in rats at 60 mg per kg per day, resulting in exposures (AUC) approximately 4 times the human exposure at the recommended daily dose. Studies in pregnant rats showed that abacavir is transferred to the fetus through the placenta. In pregnant rabbits, no developmental toxicities and no increases in fetal malformations occurred at up to the highest dose evaluated, resulting in exposures (AUC) approximately 9 times the human exposure at the recommended dose.

Lamivudine

Lamivudine was administered orally to pregnant rats (at 90, 600, and 4,000 mg per kg per day) and rabbits (at 90, 300, and 1,000 mg per kg per day and at 15, 40, and 90 mg per kg per day) during organogenesis (on Gestation Days 7 through 16 [rat] and 8 through 20 [rabbit]). No evidence of fetal malformations due to lamivudine was observed in rats and rabbits at doses producing plasma concentrations (Cmax) approximately 35 times higher than human exposure at the recommended daily dose. Evidence of early embryolethality was seen in the rabbit at systemic exposures (AUC) similar to those observed in humans, but there was no indication of this effect in the rat at plasma concentrations (Cmax) 35 times higher than human exposure at the recommended daily dose. Studies in pregnant rats showed that lamivudine is transferred to the fetus through the placenta. In the fertility/pre-and postnatal development study in rats, lamivudine was administered orally at doses of 180, 900, and 4,000 mg per kg per day (from prior to mating through postnatal Day 20). In the study, development of the offspring, including fertility and reproductive performance, was not affected by maternal administration of lamivudine.

Zidovudine

A study in pregnant rats (at 50, 150, or 450 mg per kg per day starting 26 days prior to mating through Gestation to postnatal Day 21) showed increased fetal resorptions at doses that produced systemic exposures (AUC) approximately 33 times higher than exposure at the recommended daily human dose (300 mg twice daily). However, in an oral embryo-fetal development study in rats (at 125, 250, or 500 mg per kg per day on Gestation Days 6 through 15), no fetal resorptions were observed at doses that produced systemic exposure (AUC) approximately 117 times higher than exposures at the recommended daily human dose. An oral embryo-fetal development study in rabbits (at 75, 150, or 500 mg per kg per day on gestation Days 6 through 18) showed increased fetal resorptions at the 500-mg-per-kg-per-day dose which produced systemic exposures (AUC) approximately 108 times higher than exposure at the recommended daily human dose; however, no fetal resorptions were noted at doses up to 150 mg per kg per day, which produced systemic exposure (AUC) approximately 23 times higher than exposures at the recommended daily human dose. These oral embryo-fetal development studies in the rat and rabbit revealed no evidence of fetal malformations with zidovudine. In another developmental toxicity study, pregnant rats (dosed at 3,000 mg per kg per day from Days 6 through 15 of gestation) showed marked maternal toxicity and an increased incidence of fetal malformations at exposures greater than 300 times the recommended daily human dose based on AUC. However, there were no signs of fetal malformations at doses up to 600 mg per kg per day.

8.2 Lactation

Risk Summary

The Centers for Disease Control and Prevention recommends that HIV-1-infected mothers in the United States not breastfeed their infants to avoid risking postnatal transmission of HIV-1 infection. Abacavir, lamivudine and zidovudine are present in human milk. There is no information on the effects of abacavir, lamivudine and zidovudine on the breastfed infant or the effects of the drug on milk production. Because of the potential for (1) HIV-1 transmission (in HIV-negative infants), (2) developing viral resistance (in HIV-positive infants), and (3) adverse reactions in a breastfed infant similar to those seen in adults, instruct mothers not to breastfeed if they are receiving abacavir, lamivudine and zidovudine tablets.

8.4 Pediatric Use

Abacavir, lamivudine and zidovudine tablet is not recommended in children who weigh less than 40 kg because it is a fixed-dose tablet that cannot be adjusted for these patient populations [see DOSAGE AND ADMINISTRATION (2.3)].

Therapy-Experienced Pediatric Trial

A randomized, double-blind trial, CNA3006, compared ZIAGEN® plus lamivudine and zidovudine versus lamivudine and zidovudine in pediatric subjects, most of whom were extensively pretreated with nucleoside analogue antiretroviral agents. Subjects in this trial had a limited response to abacavir.

8.5 Geriatric Use

Clinical trials of abacavir, lamivudine, and zidovudine did not include sufficient numbers of subjects aged 65 and over to determine whether they respond differently from younger subjects. In general, caution should be exercised in the administration of abacavir, lamivudine and zidovudine tablets in elderly patients reflecting the greater frequency of decreased hepatic, renal, or cardiac function, and of concomitant disease or other drug therapy [see CLINICAL PHARMACOLOGY (12.3)].

8.6 Patients with Impaired Renal Function

Abacavir, lamivudine and zidovudine tablet is not recommended for patients with creatinine clearance less than 50 mL per min because abacavir, lamivudine and zidovudine tablet is a fixed-dose combination and the dosage of the individual components cannot be adjusted. If a dose reduction of the lamivudine or zidovudine components of abacavir, lamivudine and zidovudine tablet is required for patients with renal impairment then the individual components should be used [see DOSAGE AND ADMINISTRATION (2.3), CLINICAL PHARMACOLOGY (12.3)].

8.7 Patients with Impaired Hepatic Function

Abacavir, lamivudine and zidovudine tablet is a fixed-dose combination and the dosage of the individual components cannot be adjusted. If a dose reduction of abacavir, a component of abacavir, lamivudine and zidovudine tablet, is required for patients with mild hepatic impairment (Child-Pugh Class A), then the individual components should be used [see CLINICAL PHARMACOLOGY (12.3)].

The safety, efficacy, and pharmacokinetic properties of abacavir have not been established in patients with moderate (Child-Pugh Class B) or severe (Child-Pugh Class C) hepatic impairment; therefore, abacavir, lamivudine and zidovudine tablets are contraindicated in these patients [see CONTRAINDICATIONS (4)].

Zidovudine is primarily eliminated by hepatic metabolism and zidovudine concentrations are increased in patients with impaired hepatic function, which may increase the risk of hematologic toxicity. Frequent monitoring of hematologic toxicities is advised.

10 OVERDOSAGE

There is no known specific treatment for overdose with abacavir, lamivudine and zidovudine tablets. If overdose occurs, the patient should be monitored and standard supportive treatment applied as required.

Abacavir

It is not known whether abacavir can be removed by peritoneal dialysis or hemodialysis.

Lamivudine

Because a negligible amount of lamivudine was removed via (4-hour) hemodialysis, continuous ambulatory peritoneal dialysis, and automated peritoneal dialysis, it is not known if continuous hemodialysis would provide clinical benefit in a lamivudine overdose event.

Zidovudine

Acute overdoses of zidovudine have been reported in pediatric patients and adults. These involved exposures up to 50 grams. No specific symptoms or signs have been identified following acute overdosage with zidovudine apart from those listed as adverse events such as fatigue, headache, vomiting, and occasional reports of hematological disturbances. Patients recovered without permanent sequelae. Hemodialysis and peritoneal dialysis appear to have a negligible effect on the removal of zidovudine, while elimination of its primary metabolite, 3′- azido-3′-deoxy-5′-O-β-D-glucopyranuronosylthymidine (GZDV), is enhanced.

11 DESCRIPTION

Abacavir, lamivudine and zidovudine tablets contain the following 3 synthetic nucleoside analogues: abacavir (ZIAGEN®), lamivudine (also known as EPIVIR® or 3TC), and zidovudine (also known as RETROVIR®, azidothymidine, or ZDV) with inhibitory activity against HIV-1.

Abacavir, lamivudine and zidovudine tablets are for oral administration. Each film-coated tablet contains the active ingredients 300 mg of abacavir as abacavir sulfate, 150 mg of lamivudine, and 300 mg of zidovudine, and the inactive ingredients crospovidone, magnesium stearate, microcrystalline cellulose, povidone, and yellow ferric oxide. The tablets are coated with a film opadry green that is made of FD&C blue no. 2, polyethylene glycol, polyvinyl alcohol, talc, titanium dioxide and yellow ferric oxide.

Abacavir Sulfate

The chemical name of abacavir sulfate is (1S,cis)-4-[2-amino-6-(cyclopropylamino)-9H-purin-9-yl]-2-cyclopentene-1-methanol sulfate (salt) (2:1). Abacavir sulfate is the enantiomer with 1S, 4R absolute configuration on the cyclopentene ring. It has a molecular formula of (C14H18N6O)2·H2SO4 and a molecular weight of 670.74 g per mol. It has the following structural formula:

Abacavir sulfate is a white to off-white powder and soluble in water. Dosages are expressed in terms of abacavir.

Lamivudine

The chemical name of lamivudine is (2R,cis)-4-amino-1-(2-hydroxymethyl-1,3-oxathiolan-5-yl)-(1H)-pyrimidin-2-one, 0.2 hydrate. Lamivudine is the (-) enantiomer of a dideoxy analogue of cytidine. Lamivudine has also been referred to as (-)2',3'-dideoxy, 3'-thiacytidine. It has a molecular formula of C8H11N3O3S·0.2H2O and a molecular weight of 232.86 g per mol. It has the following structural formula:

Lamivudine is a white to off-white solid and is soluble in water.

Zidovudine

The chemical name of zidovudine is 3'-azido-3'-deoxythymidine. It has a molecular formula of C10H13N5O4 and a molecular weight of 267.24 g per mol. It has the following structural formula:

Zidovudine is a white to yellowish powder with a solubility of 20.1 mg/mL in water at 25°C.

12 CLINICAL PHARMACOLOGY

12.1 Mechanism of Action

Abacavir, lamivudine and zidovudine tablet is an antiretroviral agent [see Microbiology (12.4)].

12.3 Pharmacokinetics

Pharmacokinetics in Adults

In a single-dose, 3-way crossover bioavailability trial of 1 abacavir, lamivudine and zidovudine tablet versus 1 ZIAGEN tablet (300 mg), 1 EPIVIR tablet (150 mg), plus 1 RETROVIR tablet (300 mg) administered simultaneously in healthy subjects (n = 24), there was no difference in the extent of absorption, as measured by the area under the plasma concentration-time curve (AUC) and maximal peak concentration (Cmax), of all 3 components. One abacavir, lamivudine and zidovudine tablet was bioequivalent to 1 ZIAGEN tablet (300 mg), 1 EPIVIR tablet (150 mg), plus 1 RETROVIR tablet (300 mg) following single-dose administration to fasting healthy subjects (n = 24).

Abacavir:

Following oral administration, abacavir is rapidly absorbed and extensively distributed. After oral administration of 300 mg of abacavir twice daily in 20 subjects, Cmax was 3.0 ± 0.89 mcg per mL (mean ± SD) and AUC(0 to 12 h) was 6.02 ± 1.73 mcg•hour per mL. Binding of abacavir to human plasma proteins is approximately 50% and was independent of concentration. Total blood and plasma drug-related radioactivity concentrations are identical, demonstrating that abacavir readily distributes into erythrocytes. The primary routes of elimination of abacavir are metabolism by alcohol dehydrogenase to form the 5′-carboxylic acid and glucuronyl transferase to form the 5′-glucuronide.

Lamivudine:

Following oral administration, lamivudine is rapidly absorbed and extensively distributed. Binding to plasma protein is low. Approximately 70% of an intravenous dose of lamivudine is recovered as unchanged drug in the urine. Metabolism of lamivudine is a minor route of elimination. In humans, the only known metabolite is the trans-sulfoxide metabolite (approximately 5% of an oral dose after 12 hours).

Zidovudine:

Following oral administration, zidovudine is rapidly absorbed and extensively distributed. Binding to plasma protein is low. Zidovudine is eliminated primarily by hepatic metabolism. The major metabolite of zidovudine is GZDV. GZDV AUC is about 3-fold greater than the zidovudine AUC. Urinary recovery of zidovudine and GZDV accounts for 14% and 74% of the dose following oral administration, respectively. A second metabolite, 3′-amino-3′ deoxythymidine (AMT), has been identified in plasma. The AMT AUC was one-fifth of the zidovudine AUC.

In humans, abacavir, lamivudine, and zidovudine are not significantly metabolized by CYP enzymes.

The pharmacokinetic properties of abacavir, lamivudine, and zidovudine in fasting subjects are summarized in Table 3.

Header$Parameter | Abacavir |  | Lamivudine |  | Zidovudine
Oral bioavailability (%) | 86 ± 25 | n = 6 | 86 ± 16 | n = 12 | 64 ± 10 | n = 5
Apparent volume of distribution (L/kg) | 0.86 ± 0.15 | n = 6 | 1.3 ± 0.4 | n = 20 | 1.6 ± 0.6 | n = 8
Systemic clearance (L/h/kg) | 0.80 ± 0.24 | n = 6 | 0.33 ± 0.06 | n = 20 | 1.6 ± 0.6 | n = 6
Renal clearance (L/h/kg) | 0.007 ± 0.008 | n = 6 | 0.22 ± 0.06 | n = 20 | 0.34 ± 0.05 | n = 9
Elimination half-life (h) | 1.45 ± 0.32 | n = 20 | 13 to 19b |  | 0.5 to 3b

Effect of Food on Absorption of Abacavir, Lamivudine and Zidovudine Tablets

Administration with food in a single-dose bioavailability trial resulted in lower Cmax, similar to results observed previously for the reference formulations. The average [90% CI] decrease in abacavir, lamivudine, and zidovudine Cmax was 32% [24% to 38%], 18% [10% to 25%], and 28% [13% to 40%], respectively, when administered with a high-fat meal, compared with administration under fasted conditions. Administration of abacavir, lamivudine and zidovudine tablets with food did not alter the extent of abacavir, lamivudine, and zidovudine absorption (AUC), as compared with administration under fasted conditions (n = 24) [see DOSAGE AND ADMINISTRATION (2.2)].

Specific Populations

Patients with Renal Impairment:

Abacavir, Lamivudine and Zidovudine Tablets

The effect of renal impairment on the combination of abacavir, lamivudine, and zidovudine has not been evaluated (see the U.S. prescribing information for the individual abacavir, lamivudine, and zidovudine components).

Patients with Hepatic Impairment:

Abacavir, Lamivudine and Zidovudine Tablets

The effect of hepatic impairment on the combination of abacavir, lamivudine, and zidovudine has not been evaluated (see the U.S. prescribing information for the individual abacavir, lamivudine, and zidovudine components).

Pregnant Women:

Abacavir

Abacavir pharmacokinetics were studied in 25 pregnant women during the last trimester of pregnancy receiving abacavir 300 mg twice daily. Abacavir exposure (AUC) during pregnancy was similar to those in postpartum and in HIV-infected non-pregnant historical controls. Consistent with passive diffusion of abacavir across the placenta, abacavir concentrations in neonatal plasma cord samples at birth were essentially equal to those in maternal plasma at delivery.

Lamivudine

Lamivudine pharmacokinetics were studied in 36 pregnant women during 2 clinical trials conducted in South Africa. Lamivudine pharmacokinetics in pregnant women were similar to those seen in non-pregnant adults and in postpartum women. Lamivudine concentrations were generally similar in maternal, neonatal, and umbilical cord serum samples.

Zidovudine

Zidovudine pharmacokinetics have been studied in a Phase 1 trial of 8 women during the last trimester of pregnancy. Zidovudine pharmacokinetics were similar to those of nonpregnant adults. Consistent with passive transmission of the drug across the placenta, zidovudine concentrations in neonatal plasma at birth were essentially equal to those in maternal plasma at delivery.

Although data are limited, methadone maintenance therapy in 5 pregnant women did not appear to alter zidovudine pharmacokinetics.

Geriatric Patients:

The pharmacokinetics of abacavir, lamivudine, and zidovudine have not been studied in subjects over 65 years of age.

Male and Female Patients:

There are no significant or clinically relevant gender differences in the pharmacokinetics of the individual components (abacavir, lamivudine, or zidovudine) based on the available information that was analyzed for each of the individual components.

Racial Groups:

Abacavir and Lamivudine

There are no significant or clinically relevant racial differences in pharmacokinetics of abacavir or lamivudine based on the available information that was analyzed for each of the individual components.

Zidovudine

The pharmacokinetics of zidovudine with respect to race have not been determined.

Drug Interaction Studies:

The drug interaction trials described were conducted with abacavir, lamivudine or zidovudine as single entities; no drug interaction trials have been conducted using abacavir, lamivudine and zidovudine tablets. No clinically significant drug interactions are expected between abacavir, lamivudine, and zidovudine.

Effect of Abacavir and Lamivudine on the Pharmacokinetics of Other Agents:

In vitro studies have shown that abacavir has potential to inhibit CYP1A1 and limited potential to inhibit metabolism mediated by CYP3A4. Lamivudine does not inhibit or induce CYP3A4. Abacavir and lamivudine do not inhibit or induce other CYP enzymes (such as CYP2C9, or CYP2D6). Based on in vitro study results, abacavir and lamivudine at therapeutic drug exposures are not expected to affect the pharmacokinetics of drugs that are substrates of the following transporters: organic anion transporter polypeptide (OATP)1B1/3, breast cancer resistance protein (BCRP) or P-glycoprotein (P-gp), organic cation transporter (OCT)1, OCT2, OCT3 (lamivudine only), or multidrug and toxic extrusion protein (MATE)1 and MATE2-K.

Riociguat: Coadministration of a single dose of riociguat (0.5 mg) to HIV-1–infected subjects receiving fixed-dose abacavir/dolutegravir/lamivudine is reported to increase riociguat AUC(∞) compared with riociguat AUC(∞) reported in healthy subjects due to CYP1A1 inhibition by abacavir. The exact magnitude of increase in riociguat exposure has not been fully characterized based on findings from two studies [see Drug Interactions (7.1)].

Effect of Other Agents on the Pharmacokinetics of Abacavir, Lamivudine, or Zidovudine:

Abacavir, lamivudine, and zidovudine are not significantly metabolized by CYP P450 enzymes; therefore, CYP enzyme inhibitors or inducers are not expected to affect their concentrations. In vitro, abacavir is not a substrate of OATP1B1, OATP1B3, OCT1, OCT2, OAT1, MATE1, MATE2-K, multidrug resistance-associated protein (MRP)2 or MRP4; therefore, drugs that modulate these transporters are not expected to affect abacavir plasma concentrations. Abacavir is a substrate of BCRP and P-gp in vitro; however, considering its absolute bioavailability (83%), modulators of these transporters are unlikely to result in a clinically relevant impact on abacavir concentrations.

Lamivudine is a substrate of MATE1, MATE2-K, and OCT2 in vitro. Trimethoprim (an inhibitor of these drug transporters) has been shown to increase lamivudine plasma concentrations. This interaction is not considered clinically significant as no dose adjustment of lamivudine is needed.

Lamivudine is a substrate of P-gp and BCRP; however, considering its absolute bioavailability (87%), it is unlikely that these transporters play a significant role in the absorption of lamivudine. Therefore, coadministration of drugs that are inhibitors of these efflux transporters is unlikely to affect the disposition and elimination of lamivudine.

Glucuronyl Transferase:

Due to the common metabolic pathways of abacavir and zidovudine via glucuronyl transferase, 15 HIV-1-infected subjects were enrolled in a crossover trial evaluating single doses of abacavir (600 mg), lamivudine (150 mg), and zidovudine (300 mg) alone or in combination. Analysis showed no clinically relevant changes in the pharmacokinetics of abacavir with the addition of lamivudine or zidovudine or the combination of lamivudine and zidovudine. Lamivudine exposure (AUC decreased 15%) and zidovudine exposure (AUC increased 10%) did not show clinically relevant changes with concurrent abacavir.

Ethanol:

Abacavir has no effect on the pharmacokinetic properties of ethanol. Ethanol decreases the elimination of abacavir causing an increase in overall exposure.

Interferon Alfa:

There was no significant pharmacokinetic interaction between lamivudine and interferon alfa in a trial of 19 healthy male subjects.

Methadone:

In a trial of 11 HIV-1-infected subjects receiving methadone-maintenance therapy (40 mg and 90 mg daily), with 600 mg of abacavir twice daily (twice the currently recommended dose), oral methadone clearance increased 22% (90% CI: 6% to 42%) [see DRUG INTERACTIONS (7.1)]. The addition of methadone has no clinically significant effect on the pharmacokinetic properties of abacavir.

Ribavirin:

In vitro data indicate ribavirin reduces phosphorylation of lamivudine, stavudine, and zidovudine. However, no pharmacokinetic (e.g., plasma concentrations or intracellular triphosphorylated active metabolite concentrations) or pharmacodynamic (e.g., loss of HIV-1/HCV virologic suppression) interaction was observed when ribavirin and lamivudine (n = 18), stavudine (n = 10), or zidovudine (n = 6) were coadministered as part of a multi-drug regimen to HIV-1/HCV co-infected subjects [see WARNINGS AND PRECAUTIONS (5.6)].

Sorbitol (Excipient):

Lamivudine and sorbitol solutions were coadministered to 16 healthy adult subjects in an open-label, randomized-sequence, 4-period, crossover trial. Each subject received a single 300-mg dose of lamivudine oral solution alone or coadministered with a single dose of 3.2 grams, 10.2 grams, or 13.4 grams of sorbitol in solution. Coadministration of lamivudine with sorbitol resulted in dose-dependent decreases of 20%, 39%, and 44% in the AUC (0-24); 14%, 32%, and 36% in the AUC(∞); and 28%, 52%, and 55% in the Cmax; of lamivudine, respectively.

The effects of other coadministered drugs on abacavir, lamivudine, or zidovudine are provided in Table 4.

Table 4. Effect of Coadministered Drugs on Abacavir, Lamivudine, and Zidovudine AUC [See DRUG INTERACTIONS (7) for additional information on drug interactions.]
Coadministered Drug and Dose | Drug and Dose | n | Concentrations of Abacavir, Lamivudine, or Zidovudine |  | Concentration of Coadministered Drug
 |  |  | AUC | Variability
Ethanol 0.7 g/kg | Abacavir single 600 mg | 24 | ↑41% | 90% CI: 35% to 48% | ↔ [The drug-drug interaction was only evaluated in males.]
Nelfinavir 750 mg every 8 h x 7 to 10 days | Lamivudine single 150 mg | 11 | ↑10% | 95% CI: 1% to 20% | ↔
Trimethoprim 160 mg/ Sulfamethoxazole 800 mg daily x 5 days | Lamivudine single 300 mg | 14 | ↑43% | 90% CI: 32% to 55% | ↔
Atovaquone 750 mg every 12 h with food | Zidovudine 200 mg every 8 h | 14 | ↑31% | Range: 23% to 78% [Estimated range of percent difference.] | ↔
Clarithromycin 500 mg twice daily | Zidovudine 100 mg every 4 h x 7 days | 4 | ↓12% | Range: ↓34% to ↑14% | Not Reported
Fluconazole 400 mg daily | Zidovudine 200 mg every 8 h | 12 | ↑74% | 95% CI: 54% to 98% | Not Reported
Methadone 30 to 90 mg daily | Zidovudine 200 mg every 4 h | 9 | ↑43% | Range: 16% to 64% | ↔
Nelfinavir 750 mg every 8 h x 7 to 10 days | Zidovudine single 200 mg | 11 | ↓35% | Range: 28% to 41% | ↔
Probenecid 500 mg every 6 h x 2 days | Zidovudine 2 mg/kg every 8 h x 3 days | 3 | ↑106% | Range: 100% to 170% c | Not Assessed
Rifampin 600 mg daily x 14 days | Zidovudine 200 mg every 8 h x 14 days | 8 | ↓47% | 90% CI: 41% to 53% | Not Assessed
Ritonavir 300 mg every 6 h x 4 days | Zidovudine 200 mg every 8 h x 4 days | 9 | ↓25% | 95% CI: 15% to 34% | ↔
Valproic acid 250 mg or 500 mg every 8 h x 4 days | Zidovudine 100 mg every 8 h x 4 days | 6 | ↑80% | Range: 64% to 130% | Not Assesed
↑= Increase; ↓= Decrease; ↔= No significant change; AUC = Area under the concentration versus time curve; CI = Confidence interval.

12.4 Microbiology

Mechanism of Action

Abacavir:

Abacavir is a carbocyclic synthetic nucleoside analogue. Abacavir is converted by cellular enzymes to the active metabolite, carbovir triphosphate (CBV-TP), an analogue of deoxyguanosine-5′-triphosphate (dGTP). CBV-TP inhibits the activity of HIV-1 reverse transcriptase (RT) both by competing with the natural substrate dGTP and by its incorporation into viral DNA.

Lamivudine:

Lamivudine is a synthetic nucleoside analogue. Intracellularly, lamivudine is phosphorylated to its active 5′-triphosphate metabolite, lamivudine triphosphate (3TC-TP). The principal mode of action of 3TC-TP is inhibition of RT via DNA chain termination after incorporation of the nucleotide analogue.

Zidovudine:

Zidovudine is a synthetic nucleoside analogue. Intracellularly, zidovudine is phosphorylated to its active 5′-triphosphate metabolite, zidovudine triphosphate (ZDV-TP). The principal mode of action of ZDV-TP is inhibition of RT via DNA chain termination after incorporation of the nucleotide analogue.

Antiviral Activity

Abacavir:

The antiviral activity of abacavir against HIV-1 was assessed in a number of cell lines including primary monocytes/macrophages and peripheral blood mononuclear cells (PBMCs). EC50 values ranged from 3.7 to 5.8 microM (1 microM = 0.28 mcg per mL) and 0.07 to 1.0 microM against HIV-1IIIB and HIV-1BaL, respectively, and the mean EC50 value was 0.26 + 0.18 microM against 8 clinical isolates. The median EC50 values of abacavir were 344 nM (range: 14.8 to 676 nM), 16.9 nM (range: 5.9 to 27.9 nM), 8.1 nM (range: 1.5 to 16.7 nM), 356 nM (range: 35.7 to 396 nM), 105 nM (range: 28.1 to 168 nM), 47.6 nM (range: 5.2 to 200 nM), 51.4 nM (range: 7.1 to 177 nM), and 282 nM (range: 22.4 to 598 nM) against HIV-1 clades A-G and group O viruses (n = 3 except n = 2 for clade B), respectively. The EC50 values against HIV-2 isolates (n = 4), ranged from 0.024 to 0.49 microM.

Lamivudine:

The antiviral activity of lamivudine against HIV-1 was assessed in a number of cell lines including monocytes and PBMCs using standard susceptibility assays. EC50 values were in the range of 0.003 to 15 microM (1 microM = 0.23 mcg per mL). The median EC50 values of lamivudine were 60 nM (range: 20 to 70 nM), 35 nM (range: 30 to 40 nM), 30 nM (range: 20 to 90 nM), 20 nM (range: 3 to 40 nM), 30 nM (range: 1 to 60 nM), 30 nM (range: 20 to 70 nM), 30 nM (range: 3 to 70 nM), and 30 nM (range: 20 to 90 nM) against HIV-1 clades A - G and group O viruses (n = 3 except n = 2 for clade B), respectively. The EC50 values against HIV-2 isolates (n = 4) ranged from 0.003 to 0.120 microM in PBMCs. Ribavirin (50 microM) used in the treatment of chronic HCV infection decreased the anti-HIV-1 activity of lamivudine by 3.5-fold in MT-4 cells.

Zidovudine:

The antiviral activity of zidovudine against HIV-1 was assessed in a number of cell lines including monocytes and fresh human peripheral blood lymphocytes. The EC50 and EC90 values for zidovudine were 0.01 to 0.49 microM (1 microM = 0.27 mcg per mL) and 0.1 to 9 microM, respectively. HIV-1 from therapy-naive subjects with no amino acid substitutions associated with resistance gave median EC50 values of 0.011 microM (range: 0.005 to 0.110 microM) from Virco (n = 92 baseline samples) and 0.0017 microM (range: 0.006 to 0.0340 microM) from Monogram Biosciences (n = 135 baseline samples). The EC50 values of zidovudine against different HIV-1 clades (A-G) ranged from 0.00018 to 0.02 microM, and against HIV-2 isolates from 0.00049 to 0.004 microM. Ribavirin has been found to inhibit the phosphorylation of zidovudine in cell culture.

Neither abacavir, lamivudine, nor zidovudine was antagonistic to tested anti-HIV agents, with the exception of stavudine where an antagonistic relationship with zidovudine has been demonstrated in cell culture. See full prescribing information for ZIAGEN (abacavir), EPIVIR (lamivudine), RETROVIR (zidovudine).

Resistance

HIV-1 isolates with reduced susceptibility to abacavir, lamivudine, or zidovudine have been selected in cell culture and were also recovered from subjects treated with abacavir, lamivudine, and zidovudine, or the combinations of the individual components.

Abacavir and Lamivudine:

HIV-1 isolates with reduced susceptibility to the combination of abacavir and lamivudine have been selected in cell culture with amino acid substitutions, K65R, L74V, Y115F, and M184V/I emerging in HIV-1 RT. M184V or I substitutions resulted in high-level resistance to lamivudine and an approximately 2-fold decrease in susceptibility to abacavir. Substitutions K65R, L74M, or Y115F with M184V or I conferred a 7- to 8-fold reduction in abacavir susceptibility, and combinations of three substitutions were required to confer more than an 8-fold reduction in susceptibility.

Zidovudine:

Genotypic analyses of the isolates selected in cell culture and recovered from zidovudine-treated subjects showed thymidine analogue mutation (TAM) substitutions in HIV-1 RT (M41L, D67N, K70R, L210W, T215Y or F, and K219E/R/H/Q/N) that confer zidovudine resistance. In general, higher levels of resistance were associated with a greater number of substitutions. In some subjects harboring zidovudine-resistant virus at baseline, phenotypic sensitivity to zidovudine was restored by 12 weeks of treatment with lamivudine and zidovudine.

Cross-Resistance

Cross-resistance has been observed among NRTIs. The combination of abacavir/lamivudine has demonstrated decreased susceptibility to viruses with a K65R substitution with or without an M184V/I substitution, viruses with L74V plus the M184V/I substitution, and viruses with TAM substitutions (M41L, D67N, K70R, L210W, T215Y/F, K219 E/R/H/Q/N) plus M184V. An increasing number of TAMs is associated with a progressive reduction in abacavir susceptibility.

TAMs are selected by zidovudine and confer cross-resistance to abacavir, didanosine, stavudine, and tenofovir. Cross-resistance between lamivudine and zidovudine has not been reported.

13 NONCLINICAL TOXICOLOGY

13.1 Carcinogenesis, Mutagenesis, Impairment of Fertility

Carcinogenicity

Abacavir:

Abacavir was administered orally at 3 dosage levels to separate groups of mice and rats in 2-year carcinogenicity studies. Results showed an increase in the incidence of malignant and non-malignant tumors. Malignant tumors occurred in the preputial gland of males and the clitoral gland of females of both species, and in the liver of female rats. In addition, non-malignant tumors also occurred in the liver and thyroid gland of female rats. These observations were made at systemic exposures in the range of 6 to 32 times the human exposure at the recommended dose of 600 mg.

Lamivudine:

Long-term carcinogenicity studies with lamivudine in mice and rats showed no evidence of carcinogenic potential at exposures up to 10 times (mice) and 58 times (rats) the human exposures at the recommended dose of 300 mg.

Zidovudine:

Zidovudine was administered orally at 3 dosage levels to separate groups of mice and rats (60 females and 60 males in each group). Initial single daily doses were 30, 60, and 120 mg per kg per day in mice and 80, 220, and 600 mg per kg per day in rats. The doses in mice were reduced to 20, 30, and 40 mg per kg per day after Day 90 because of treatment-related anemia, whereas in rats only the high dose was reduced to 450 mg per kg per day on Day 91 and then to 300 mg per kg per day on Day 279.

In mice, 7 late-appearing (after 19 months) vaginal neoplasms (5 non-metastasizing squamous cell carcinomas, 1 squamous cell papilloma, and 1 squamous polyp) occurred in animals given the highest dose. One late-appearing squamous cell papilloma occurred in the vagina of a middle-dose animal. No vaginal tumors were found at the lowest dose.

In rats, 2 late-appearing (after 20 months), non-metastasizing vaginal squamous cell carcinomas occurred in animals given the highest dose. No vaginal tumors occurred at the low or middle dose in rats. No other drug-related tumors were observed in either sex of either species.

At doses that produced tumors in mice and rats, the estimated drug exposure (as measured by AUC) was approximately 3 times (mouse) and 24 times (rat) the estimated human exposure at the recommended therapeutic dose of 100 mg every 4 hours.

It is not known how predictive the results of rodent carcinogenicity studies may be for humans.

Two transplacental carcinogenicity studies were conducted in mice. One study administered zidovudine at doses of 20 mg per kg per day or 40 mg per kg per day from gestation Day 10 through parturition and lactation with dosing continuing in offspring for 24 months postnatally. At these doses, exposures were approximately 3 times the estimated human exposure at the recommended doses. After 24 months at the 40-mg-per-kg-per-day dose, an increase in incidence of vaginal tumors was noted with no increase in tumors in the liver or lung or any other organ in either gender. These findings are consistent with results of the standard oral carcinogenicity study in mice, as described earlier. A second study administered zidovudine at maximum tolerated doses of 12.5 mg per day or 25 mg per day (approximately 1,000 mg per kg nonpregnant body weight or approximately 450 mg per kg of term body weight) to pregnant mice from Days 12 through 18 of gestation. There was an increase in the number of tumors in the lung, liver, and female reproductive tracts in the offspring of mice receiving the higher dose level of zidovudine.

Mutagenicity

Abacavir:

Abacavir induced chromosomal aberrations both in the presence and absence of metabolic activation in an in vitro cytogenetic study in human lymphocytes. Abacavir was mutagenic in the absence of metabolic activation, although it was not mutagenic in the presence of metabolic activation in an L5178Y mouse lymphoma assay. Abacavir was clastogenic in males and not clastogenic in females in an in vivo mouse bone marrow micronucleus assay. Abacavir was not mutagenic in bacterial mutagenicity assays in the presence and absence of metabolic activation.

Lamivudine:

Lamivudine was mutagenic in an L5178Y mouse lymphoma assay and clastogenic in a cytogenetic assay using cultured human lymphocytes. Lamivudine was not mutagenic in a microbial mutagenicity assay, in an in vitro cell transformation assay, in a rat micronucleus test, in a rat bone marrow cytogenetic assay, and in an assay for unscheduled DNA synthesis in rat liver.

Zidovudine:

Zidovudine was mutagenic in an L5178Y mouse lymphoma assay, positive in an in vitro cell transformation assay, clastogenic in a cytogenetic assay using cultured human lymphocytes, and positive in mouse and rat micronucleus tests after repeated doses. It was negative in a cytogenetic study in rats given a single dose.

Impairment of Fertility

Abacavir:

Abacavir did not affect male or female fertility in rats at a dose associated with exposures (AUC) approximately 3.3 times (male) or 4.1 times (female) those in humans at the clinically recommended dose.

Lamivudine:

Lamivudine did not affect male or female fertility in rats at doses up to 4,000 mg per kg per day, associated with concentrations approximately 42 times (male) or 63 times (female) higher than the concentrations (Cmax) in humans at the dose of 300 mg.

Zidovudine:

Zidovudine, administered to male and female rats at doses up to 450 mg per kg per day, which is 7 times the recommended adult dose (300 mg twice daily) based on body surface area, had no effect on fertility based on conception rates.

13.2 Animal Toxicology and/or Pharmacology

Myocardial degeneration was found in mice and rats following administration of abacavir for 2 years. The systemic exposures were equivalent to 7 to 24 times the expected systemic exposure in humans at a dose of 600 mg. The clinical relevance of this finding has not been determined.

14 CLINICAL STUDIES

The following trial was conducted with the individual components of abacavir, lamivudine and zidovudine tablet [see CLINICAL PHARMACOLOGY (12.3)].

CNA3005 was a multicenter, double-blind, controlled trial in which 562 HIV-1-infected, therapy-naive adults were randomized to receive either ZIAGEN (300 mg twice daily) plus COMBIVIR (lamivudine 150 mg/zidovudine 300 mg twice daily), or indinavir (800 mg 3 times a day) plus COMBIVIR twice daily. The trial was stratified at randomization by pre-entry plasma HIV-1 RNA 10,000 to 100,000 copies per mL and plasma HIV-1 RNA greater than 100,000 copies per mL. Trial participants were male (87%), Caucasian (73%), black (15%), and Hispanic (9%). At baseline the median age was 36 years; the median pretreatment CD4+ cell count was 360 cells per mm^3, and median plasma HIV-1 RNA was 4.8 log10 copies per mL. Proportions of subjects with plasma HIV-1 RNA less than 400 copies per mL (using Roche AMPLICOR HIV-1 MONITOR Test) through 48 weeks of treatment are summarized in Table 5.

Header$Outcome | ZIAGEN plus Lamivudine/Zidovudine (n = 262) | Indinavir plus Lamivudine/Zidovudine (n = 265)
Respondera | 49% | 50%
Virologic failureb | 31% | 28%
Discontinued due to adverse reactions | 10% | 12%
Discontinued due to other reasonsc | 11% | 10%

Treatment response by plasma HIV-1 RNA strata is shown in Table 6.

Table 6. Proportions of Responders through Week 48 by Screening Plasma HIV-1 RNA Levels (CNA3005)
Screening HIV-1 RNA (copies/mL) | ZIAGEN® plus Lamivudine/Zidovudine (n = 262) |  | Indinavir plus Lamivudine/Zidovudine (n = 265)
 | <400 copies/mL | n | <400 copies/mL | n
≥10,000 to ≤100,000 | 50% | 166 | 48% | 165
>100,000 | 48% | 96 | 52% | 100

In subjects with baseline viral load greater than 100,000 copies per mL, percentages of subjects with HIV-1 RNA levels less than 50 copies per mL were 31% in the group receiving abacavir vs. 45% in the group receiving indinavir.

Through Week 48, an overall mean increase in CD4+ cell count of about 150 cells per mm3 was observed in both treatment arms. Through Week 48, 9 subjects (3.4%) in the group receiving abacavir (6 CDC classification C events and 3 deaths) and 3 subjects (1.5%) in the group receiving indinavir (2 CDC classification C events and 1 death) experienced clinical disease progression.

29 a Subjects achieved and maintained confirmed HIV-1 RNA less than 400 copies per mL.

16 HOW SUPPLIED/STORAGE AND HANDLING

Abacavir, lamivudine and zidovudine is available as tablets. Each tablet contains 300 mg of abacavir as abacavir sulfate, 150 mg of lamivudine, and 300 mg of zidovudine. The tablets are blue-green colored, oval shaped, biconvex, film-coated, debossed with "LU" on one side and "N51" on the other side. They are packaged as follows:

Bottles of 60 Tablets NDC 68180-286-07

Bottles of 100 Tablets NDC 68180-286-01

Bottles of 500 Tablets NDC 68180-286-02

Store at 25°C (77°F); excursions permitted to 15° to 30°C (59° to 86°F) [see USP Controlled Room Temperature].

17 PATIENT COUNSELING INFORMATION

Advise the patient to read the FDA-approved patient labeling (Medication Guide).

Hypersensitivity Reaction

Inform patients:

- that a Medication Guide and Warning Card summarizing the symptoms of the abacavir hypersensitivity reaction and other product information will be dispensed by the pharmacist with each new prescription and refill of abacavir, lamivudine and zidovudine tablet, and instruct the patient to read the Medication Guide and Warning Card every time to obtain any new information that may be present about abacavir, lamivudine and zidovudine tablets. The complete text of the Medication Guide is reprinted at the end of this document.
- to carry the Warning Card with them.
- how to identify a hypersensitivity reaction [see WARNINGS AND PRECAUTIONS (5.1), MEDICATION GUIDE] .
- that if they develop symptoms consistent with a hypersensitivity reaction they should call their healthcare provider right away to determine if they should stop taking abacavir, lamivudine and zidovudine tablet.
- that a hypersensitivity reaction can worsen and lead to hospitalization or death if abacavir, lamivudine and zidovudine tablet is not immediately discontinued.
- to not restart abacavir, lamivudine and zidovudine tablet or any other abacavir-containing product following a hypersensitivity reaction because more severe symptoms can occur within hours and may include life-threatening hypotension and death.
- that if they have a hypersensitivity reaction, they should dispose of any unused abacavir, lamivudine and zidovudine tablet to avoid restarting abacavir.
- that a hypersensitivity reaction is usually reversible if it is detected promptly and abacavir, lamivudine and zidovudine tablet is stopped right away.
- that if they have interrupted abacavir, lamivudine and zidovudine tablet for reasons other than symptoms of hypersensitivity (for example, those who have an interruption in drug supply), a serious or fatal hypersensitivity reaction may occur with reintroduction of abacavir.
- to not restart abacavir, lamivudine and zidovudine tablet or any other abacavir-containing product without medical consultation and only if medical care can be readily accessed by the patient or others.

Neutropenia and Anemia

Inform patients that the important toxicities associated with zidovudine are neutropenia and/or anemia. Inform them of the extreme importance of having their blood counts followed closely while on therapy, especially for patients with advanced HIV-1 disease [see BOXED WARNING, WARNINGS AND PRECAUTIONS (5.2)].

Myopathy

Inform patients that myopathy and myositis with pathological changes, similar to that produced by HIV-1 disease, have been associated with prolonged use of zidovudine [see WARNINGS AND PRECAUTIONS (5.3)].

Lactic Acidosis/Hepatomegaly with Steatosis

Advise patients that lactic acidosis and severe hepatomegaly with steatosis have been reported with use of nucleoside analogues and other antiretrovirals. Advise patients to stop taking abacavir, lamivudine and zidovudine tablets if they develop clinical symptoms suggestive of lactic acidosis or pronounced hepatotoxicity [see WARNINGS AND PRECAUTIONS (5.4)].

Patients with Hepatitis B or C Co-infection

Advise patients co-infected with HIV-1 and HBV that worsening of liver disease has occurred in some cases when treatment with lamivudine was discontinued. Advise patients to discuss any changes in regimen with their healthcare provider [see WARNINGS AND PRECAUTIONS (5.5)].

Inform patients with HIV-1/HCV co-infection that hepatic decompensation (some fatal) has occurred in HIV-1/HCV co-infected patients receiving combination antiretroviral therapy for HIV-1 and interferon alfa with or without ribavirin [see WARNINGS AND PRECAUTIONS (5.6)].

Drug Interactions

Advise patients that other medications may interact with abacavir, lamivudine and zidovudine tablets and certain medications, including ganciclovir, interferon alfa, and ribavirin, may exacerbate the toxicity of zidovudine, a component of abacavir, lamivudine and zidovudine tablets [see DRUG INTERACTIONS (7.3)].

Immune Reconstitution Syndrome

Advise patients to inform their healthcare provider immediately of any signs and symptoms of infection as inflammation from previous infection may occur soon after combination antiretroviral therapy, including when abacavir, lamivudine and zidovudine tablets are started [see WARNINGS AND PRECAUTIONS (5.7)].

Lipoatrophy

Advise patients that loss of subcutaneous fat may occur in patients receiving abacavir, lamivudine and zidovudine tablets and that they will be regularly assessed during therapy [see WARNINGS AND PRECAUTIONS (5.8)].

Pregnancy Registry

Advise patients that there is a pregnancy exposure registry that monitors pregnancy outcomes in women exposed to abacavir, lamivudine and zidovudine tablets during pregnancy [see USE IN SPECIFIC POPULATIONS (8.1)].

Lactation

Instruct women with HIV-1 infection not to breastfeed because HIV-1 can be passed to the baby in the breast milk [see USE IN SPECIFIC POPULATIONS (8.2)].

Missed Dose

Instruct patients that if they miss a dose of abacavir, lamivudine and zidovudine tablets, to take it as soon as they remember. Advise patients not to double their next dose or take more than the prescribed dose [see DOSAGE AND ADMINISTRATION (2)].

Availability of Medication Guide

Instruct patients to read the Medication Guide before starting abacavir, lamivudine and zidovudine tablets and to re-read it each time the prescription is renewed. Instruct patients to inform their physician or pharmacist if they develop any unusual symptom, or if any known symptom persists or worsens.

The brands listed are trademarks of their respective owners and are not trademarks of Lupin Pharmaceuticals, Inc. The makers of these brands are not affiliated with and do not endorse Lupin Pharmaceuticals, Inc. or its products.

Manufactured for:

Lupin Pharmaceuticals, Inc.

Baltimore, Maryland 21202

United States

Manufactured by:

Lupin Limited

Pithampur (M.P.) - 454 775

India

Revised: May 2021 ID#: 267549

MEDICATION GUIDE

MEDICATION GUIDE

Abacavir, Lamivudine and Zidovudine Tablets

(a-BAK-a-vir , la-MIV-ue-deen, zye-DOE-vue-deen)

What is the most important information I should know about abacavir, lamivudine and zidovudine tablets?

Abacavir, lamivudine and zidovudine tablets can cause serious side effects, including:

- Serious allergic reactions (hypersensitivity reaction) that can cause death have happened with abacavir, lamivudine and zidovudine tablets and other abacavir-containing products. Your risk of this allergic reaction is much higher if you have a gene variation called HLA-B*5701. Your healthcare provider can determine with a blood test if you have this gene variation.

If you get a symptom from 2 or more of the following groups while taking abacavir, lamivudine and zidovudine tablets, call your healthcare provider right away to find out if you should stop taking abacavir, lamivudine and zidovudine tablets.

 | Symptom (s)
Group 1 | Fever
Group 2 | Rash
Group 3 | Nausea, vomiting, diarrhea, abdominal (stomach area) pain
Group 4 | Generally ill feeling, extreme tiredness, or achiness
Group 5 | Shortness of breath, cough, sore throat

A list of these symptoms is on the Warning Card your pharmacist gives you. Carry this Warning Card with you at all times.

If you stop abacavir, lamivudine and zidovudine tablets because of an allergic reaction, never take abacavir, lamivudine and zidovudine tablets or any other abacavir-containing medicine (EPZICOM®, TRIUMEQ®, or ZIAGEN®) again.

- If you have an allergic reaction, dispose of any unused abacavir, lamivudine and zidovudine tablets. Ask your pharmacist how to properly dispose of medicines.
- If you take abacavir, lamivudine and zidovudine tablets or any other abacavir-containing medicine again after you have had an allergic reaction, within hours you may get life-threatening symptoms that may include very low blood pressure or death .
- If you stop abacavir, lamivudine and zidovudine tablets for any other reason, even for a few days, and you are not allergic to abacavir, lamivudine and zidovudine tablets, talk with your healthcare provider before taking it again. Taking abacavir, lamivudine and zidovudine tablets again can cause a serious allergic or life-threatening reaction, even if you never had an allergic reaction to it before.

If your healthcare provider tells you that you can take abacavir, lamivudine and zidovudine tablets again, start taking it when you are around medical help or people who can call a healthcare provider if you need one.

- Blood problems. Zidovudine, one of the medicines in abacavir, lamivudine and zidovudine tablets, can cause serious blood cell problems. These include reduced numbers of white blood cells (neutropenia) and extremely reduced numbers of red blood cells (anemia). These blood cell problems are especially likely to happen in people with advanced human immunodeficiency virus 1 (HIV-1) infection or Acquired Immune Deficiency Syndrome (AIDS). Your healthcare provider should check your blood cell counts regularly during treatment with abacavir, lamivudine and zidovudine tablets.
- Muscle pain or weakness can happen during treatment with abacavir, lamivudine and zidovudine tablets. Zidovudine one of the medicines in abacavir, lamivudine and zidovudine tablets, can cause muscle pain or weakness when used for a long time.
- Too much Lactic acid in your blood (lactic acidosis). Lactic acidosis is a serious medical emergency that can lead to death. Call your healthcare provider right away if you get any of the following symptoms that could be signs of lactic acidosis:
  - feel very weak or tired
  - unusual (not normal) muscle pain
  - trouble breathing
  - stomach pain with nausea and vomiting
  - feel cold, especially in your arms and legs
  - feel dizzy or light-headed
  - have a fast or irregular heartbeat
- Severe liver problems in some cases, these serious liver problems can lead to death. Your liver may become large (hepatomegaly) and you may develop fat in your liver (steatosis). Call your healthcare provider right away if you get any of the following signs or symptoms of liver problems:
  - your skin or the white part of your eyes turns yellow (jaundice)
  - dark or "tea-colored" urine
  - light colored stools (bowel movements)
  - loss of appetite for several days or longer
  - nausea
  - pain, aching, or tenderness on the right side of your stomach area

You may be more likely to get lactic acidosis or serious liver problems if you are female or very overweight (obese).

- Worsening of hepatitis B virus (HBV) infection. HBV infection and take abacavir, lamivudine and zidovudine tablets your HBV may get worse (flare-up) if you stop taking abacavir, lamivudine and zidovudine tablets. A "flare-up" is when your HBV infection suddenly returns in a worse way than before.
- $$UnOrderedlist
- Do not run out of abacavir, lamivudine and zidovudine tablets. Refill your prescription or talk to your healthcare provider before your abacavir, lamivudine and zidovudine tablets are all gone.
- Do not stop abacavir, lamivudine and zidovudine tablets without first talking to your healthcare provider.
- If you stop taking abacavir, lamivudine and zidovudine tablets, your healthcare provider will need to check your health often and do blood tests regularly for several months to check your liver function and monitor your HBV infection. It may be necessary to give you a medicine to treat HBV. Tell your healthcare provider about any new or unusual symptoms you may have after you stop taking abacavir, lamivudine and zidovudine tablets.
- $$EndUnOrderedlist
- Resistant HBV. If you have HIV-1 and HBV, the HBV can change (mutate) during your treatment with abacavir, lamivudine and zidovudine tablets and become harder to treat (resistant).
- Use with interferon and ribavirin-based regimens. Worsening of liver disease that has caused death has happened in people infected with both HIV-1 and hepatitis C virus who are taking HIV-1 medicines and are also being treated for hepatitis C with interferon alfa with or without ribavirin. If you are taking abacavir, lamivudine and zidovudine tablets and interferon alfa with or without ribavirin, tell your healthcare provider if you have any new symptoms.
- For more information about side effects, see "What are the possible side effects of abacavir, lamivudine and zidovudine tablets.

What are abacavir, lamivudine and zidovudine tablets?

Abacavir, lamivudine and zidovudine tablet is a prescription medicine used alone or with other HIV-1 medicines to treat HIV-1 infection. HIV-1 is the virus that causes AIDS. Abacavir, lamivudine and zidovudine tablet contains the prescription medicines, abacavir , lamivudine and zidovudine .

Abacavir, lamivudine and zidovudine tablets should not be used in children weighing less than 88 pounds (40 kg).

Do not take abacavir, lamivudine and zidovudine tablets if you:

- have a certain type of gene variation called the HLA-B*5701 allele. Your healthcare provider will test you for this before prescribing treatment with abacavir, lamivudine and zidovudine tablets.
- are allergic to abacavir, lamivudine, zidovudine or any of the ingredients in abacavir, lamivudine and zidovudine tablets. See the end of this Medication Guide for a complete list of ingredients in abacavir, lamivudine and zidovudine tablets.
- have certain liver problems.

Before you take abacavir, lamivudine and zidovudine tablets, tell your healthcare provider about all of your medical conditions, includingif you:

- have been tested and know whether or not you have a particular gene variation called HLA-B*5701.
- have or have had liver problems, including hepatitis B or C virus infection.
- have kidney problems.
- have low blood cell counts (bone marrow problem). Ask your healthcare provider if you are not sure.
- have heart problems, smoke, or have diseases that increase your risk of heart disease such as high blood pressure, high cholesterol, or diabetes.
- are pregnant or plan to become pregnant.

Pregnancy Registry. There is a pregnancy registry for women who take HIV-1 medicines during pregnancy. The purpose of this registry is to collect information about the health of you and your baby. Talk to your healthcare provider about how you can take part in this registry.

- are breastfeeding or plan to breastfeed. Do not breastfeed if you take abacavir, lamivudine and zidovudine tablets.
  - You should not breastfeed if you have HIV-1 because of the risk of passing HIV-1 to your baby.

Tell your healthcare provider about all the medicines you take, including prescription and over-the- counter medicines, vitamins, and herbal supplements.

Some medicines interact with abacavir, lamivudine and zidovudine tablets. Keep a list of your medicines to show your healthcare provider and pharmacist when you get a new medicine. You can ask your healthcare provider or pharmacist for a list of medicines that interact with abacavir, lamivudine and zidovudine tablets.

Do not start taking a new medicine without telling your healthcare provider. Your healthcare provider can tell you if it is safe to take abacavir, lamivudine and zidovudine tablets with other medicines.

How should I take abacavir, lamivudine and zidovudine tablets?

- Take abacavir, lamivudine and zidovudine tablets exactly as your healthcare provider tells you to take it.
- Do not change your dose or stop taking abacavir, lamivudine and zidovudine tablets without talking with your healthcare provider.
- If you miss a dose of abacavir, lamivudine and zidovudine tablets, take it as soon as you remember. Do not take 2 doses at the same time or take more than your healthcare provider tells you to take.
- Stay under the care of a healthcare provider during treatment with abacavir, lamivudine and zidovudine tablets.
- Abacavir, lamivudine and zidovudine tablets may be taken with or without food.
- Do not run out of abacavir, lamivudine and zidovudine tablets. The virus in your blood may increase and the virus may become harder to treat. When your supply starts to run low, get more from your healthcare provider or pharmacy.
- If you take too much abacavir, lamivudine and zidovudine tablets, call your healthcare provider or go to the nearest hospital emergency room right away.

What are the possible side effects of abacavir, lamivudine and zidovudine tablets?

- Abacavir, lamivudine and zidovudine tablets can cause serious side effects including :
- See "What is the most important information I should know about abacavir, lamivudine and zidovudine tablets?"
- Changes in your immune system (Immune Reconstitution Syndrome) can happen when you start taking HIV-1 medicines. Your immune system may get stronger and begin to fight infections that have been hidden in your body for a long time. Tell your healthcare provider right away if you start having new symptoms after you start taking abacavir, lamivudine and zidovudine tablets.
- Loss of body fat can happen in people who take HIV-1 medicines that contain zidovudine. This loss of fat may occur in the legs, arms, buttocks, and face. The loss of fat may be permanent and long-term health effects are not known.
- Heart attack Some HIV-1 medicines including abacavir, lamivudine and zidovudine tablets may increase your risk of heart attack.

The most common side effects of abacavir, lamivudine and zidovudine tablets include:

- nausea
- headache
- weakness or tiredness
- vomiting

Tell your healthcare provider if you have any side effect that bothers you or that does not go away.

These are not all the possible side effects of abacavir, lamivudine and zidovudine tablets. Call your doctor for medical advice about side effects. You may report side effects to FDA at 1-800-FDA-1088.

How should I store abacavir, lamivudine and zidovudine tablets?

- Store abacavir, lamivudine and zidovudine tablets at room temperature.

Keep abacavir, lamivudine and zidovudine tablets and all medicines out of the reach of children.

General information for safe and effective use of abacavir, lamivudine and zidovudine tablets.

Medicines are sometimes prescribed for purposes other than those listed in a Medication Guide. Do not use abacavir, lamivudine and zidovudine tablets for a condition for which it was not prescribed. Do not give abacavir, lamivudine and zidovudine tablets to other people, even if they have the same symptoms that you have. It may harm them.

You can ask your healthcare provider or pharmacist for the information about abacavir, lamivudine and zidovudine tablets that is written for health professionals.

What are the ingredients in abacavir, lamivudine and zidovudine tablets?

Active ingredients: abacavir, lamivudine and zidovudine

Inactive ingredients: crospovidone, magnesium stearate, microcrystalline cellulose, povidone, and yellow ferric oxide.

Tablet film coating contains: opadry green made of FD&C blue no. 2, polyethylene glycol, polyvinyl alcohol, talc, titanium dioxide and yellow ferric oxide.

This Medication Guide has been approved by the U.S. Food and Drug Administration.

The brands listed are trademarks of their respective owners and are not trademarks of Lupin Pharmaceuticals, Inc. The makers of these brands are not affiliated with and do not endorse Lupin Pharmaceuticals, Inc. or its products.

Manufactured for:

Lupin Pharmaceuticals, Inc.

Baltimore, Maryland 21202

United States

Manufactured by:

Lupin Limited

Pithampur (M.P.) - 454 775

India

Revised: May 2021 ID#: 267580

For more information go to www.lupinpharmaceuticals.com or call 1-800-399-2561.

PACKAGE LABEL

ABACAVIR, LAMIVUDINE AND ZIDOVUDINE TABLETS

300 mg 150 mg 300 mg

Rx only

NDC 68180-286-07

Notice to Authorized Dispenser:

Dispense drug product with Medication Guide and Warning Card from the carton.

Each tablet contains abacavir sulfate USP equivalent to 300 mg of abacavir, 150 mg of lamivudine USP, and 300 mg of zidovudine USP.

Store at 25°C (77°F); excursions permitted to 15° to 30°C (59° to 86°F) [see USP Controlled Room Temperature].

See prescribing information for dosage information.

Manufactured for:

Lupin Pharmaceuticals, Inc.

Baltimore, Maryland 21202

United States

Manufactured by:

Lupin Limited

Pithampur (M.P.) - 454 775

INDIA